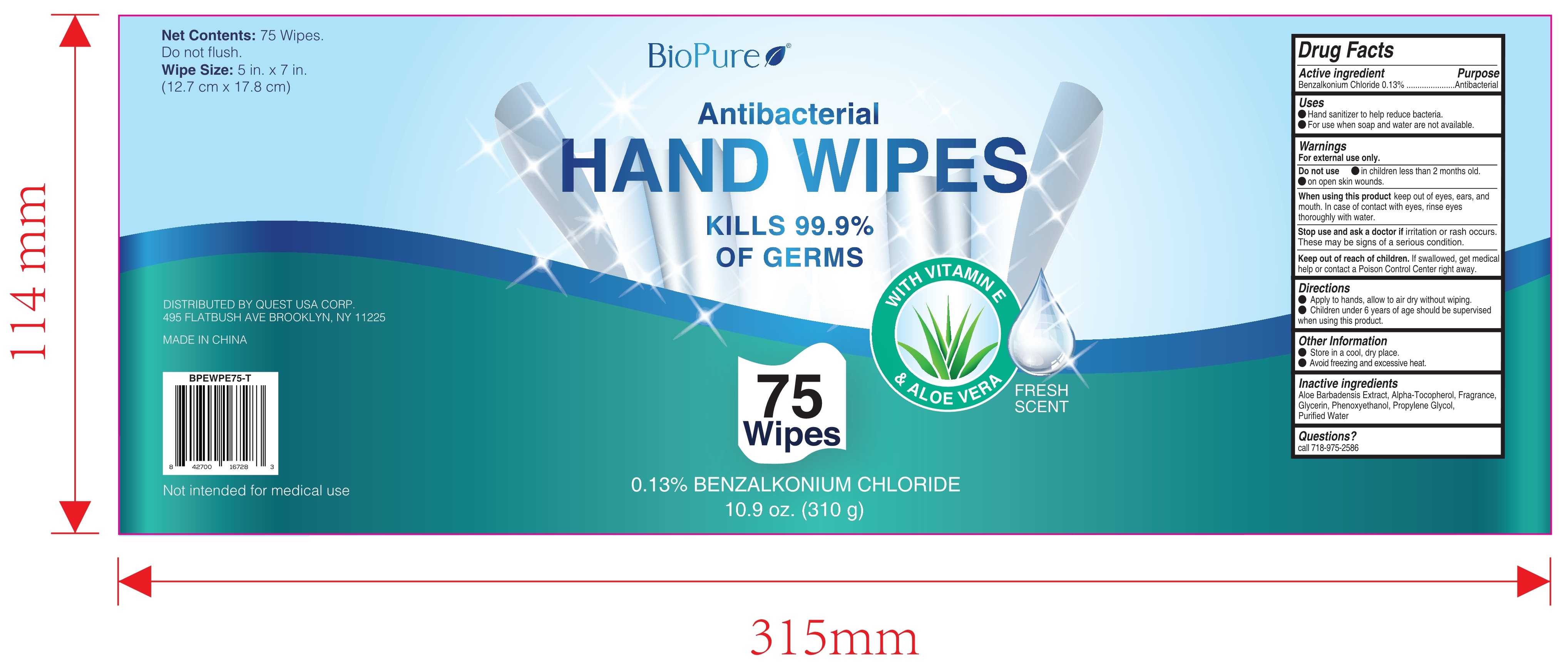 DRUG LABEL: Antibacterial Hand Wipes
NDC: 79866-008 | Form: CLOTH
Manufacturer: Osike Cosmetics Co., Ltd.
Category: otc | Type: HUMAN OTC DRUG LABEL
Date: 20220120

ACTIVE INGREDIENTS: BENZALKONIUM CHLORIDE 0.13 g/100 1
INACTIVE INGREDIENTS: FRAGRANCE CLEAN ORC0600327; PROPYLENE GLYCOL; WATER; ALPHA-TOCOPHEROL; GLYCERIN; PHENOXYETHANOL; ALOE VERA LEAF

79866-008
Antibacterial Hand Wipes

Active Ingredient(s)

Benzalkonium Chloride 0.13%

Use

●Hand sanitizer to help reduce bacteria
●For use when soap and water are not available.

Warnings

For external use only.

Do not use
●in children less than 2 months old.
●on open skin wounds

When using this product keep out of eyes, ears, and mouth. In case of contact with eyes, rinse eyes thoroughly with water.

Stop use and ask a doctor if irritation or rash occurs. These may be signs of a serious condition

Keep out of reach of children. If swallowed. get medical help or contact a Poison Control Center right away.

Do not use

●in children less than 2 months old.
●on open skin wounds

When using this product keep out of eyes, ears, and mouth. In case of contact with eyes, rinse eyes thoroughly with water.

Stop use and ask a doctor if irritation or rash occurs. These may be signs of a serious condition

Keep out of reach of children. If swallowed. get medical help or contact a Poison Control Center right away.

Stop use and ask a doctor if irritation or rash occurs. These may be signs of a serious condition

Keep out of reach of children. If swallowed. get medical help or contact a Poison Control Center right away.

Directions

●Apply to hands, allow to air dry without wiping.
●Children under 6 years of age should be supervised when using this product

Other information

●Store in a cool, dry place.
●Avoid freezing and excessive heat.

Inactive ingredients

Aloe Barbadensis Extract, Alpha-Tocopherol, Fragrance, Glycerin, Phenoxyethanol, Propylene Glycol, Purified Water